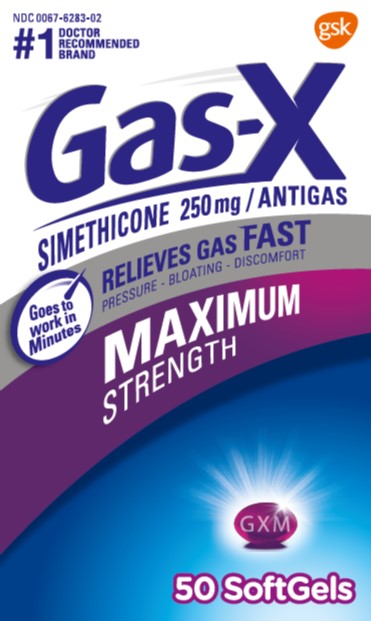 DRUG LABEL: Gas-X

NDC: 0067-6283 | Form: CAPSULE, LIQUID FILLED
Manufacturer: Haleon US Holdings LLC
Category: otc | Type: HUMAN OTC DRUG LABEL
Date: 20240405

ACTIVE INGREDIENTS: DIMETHICONE 250 mg/1 1
INACTIVE INGREDIENTS: D&C RED NO. 33; FD&C BLUE NO. 1; GELATIN, UNSPECIFIED; GLYCERIN; LECITHIN, SOYBEAN; WATER; TITANIUM DIOXIDE

Drug Facts

Active ingredient (in each softgel)

Simethicone 250 mg

Purpose

Antigas

Use

for the relief of

- pressure, bloating, and fullness commonly referred to as gas

Directions

- adults and children 12 years and older: swallow with water 1 or 2 softgels as needed after meals and at bedtime
- do not exceed 2 softgels in 24 hours except under the advice and supervision of a physician

Other information

- store at a controlled room temperature 20-25°C (68-77°F)
- protect from light heat and moisture

Inactive ingredients

D&C red no. 33, FD&C blue no. 1, gelatin, glycerin, lecithin, purified water, titanium dioxide

Questions or comments?

Call 1-800-328-5204

Principal Display Panel

NEW

#1 DOCTOR RECOMMENDED BRAND

NDC 0067-6283-02

Gas-X

SIMETHICONE 250 mg/ ANTIGAS

Goes to work in Minutes

RELIEVES GAS FAST

PRESSURE • BLOATING • DISCOMFORT

MAXIMUM STRENGTH

50 SoftGels

Gas-X Maximum StrengthSoftgels are concentrated to contain liquid gas-fighting medicine in a small softgel so they are easy to swallow, and there is no chalky taste.

TAMPER EVIDENT FEATURE:

Do not use if blister is broken or damaged.

Gas-X®Ultra Strength Softgels offer fast, effective relief of pressure and bloating that antacids can’t provide. They are specially formulated with simethicone, the antigas medicine doctors recommend most for pressure, bloating or discomfort referred to as gas.

1-800-328-5204

www.Gas-X.com

Distributed by:

GSK Consumer Healthcare

- Warren, NJ 07059

©2020 GSK group of companies or its licensor.

Trademarks are owned by or licensed to the GSK group of companies.

1000610